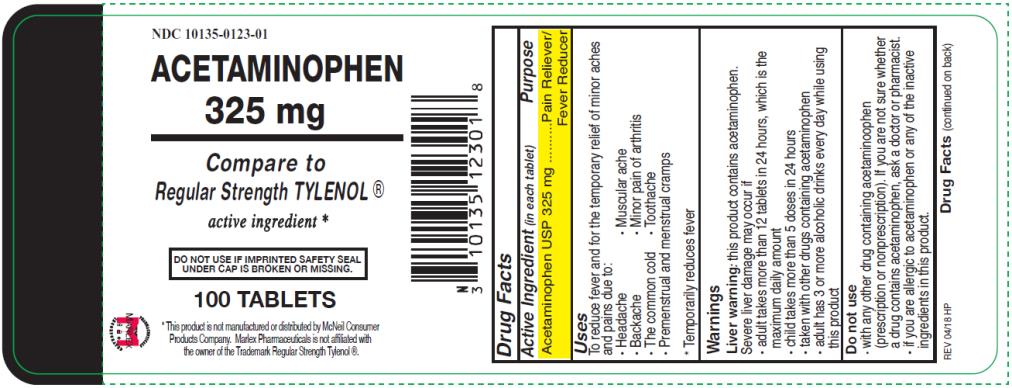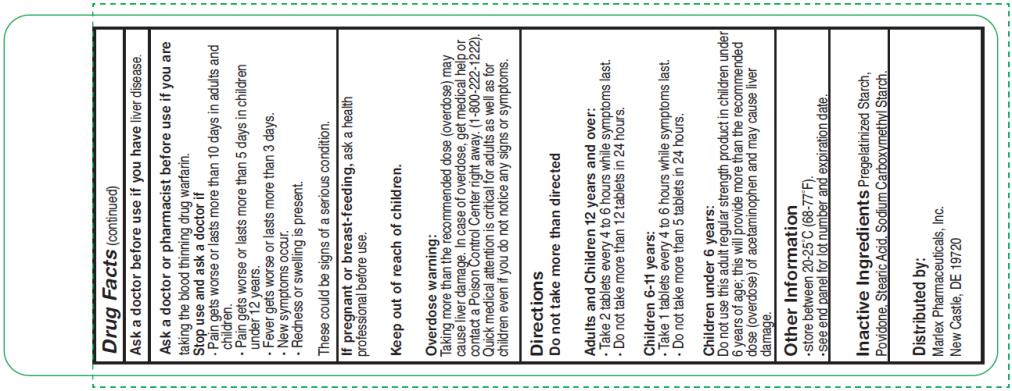 DRUG LABEL: Acetaminophen 325mg
NDC: 10135-123 | Form: TABLET
Manufacturer: Marlex Pharmaceuticals Inc
Category: otc | Type: HUMAN OTC DRUG LABEL
Date: 20210203

ACTIVE INGREDIENTS: ACETAMINOPHEN 325 mg/1 1
INACTIVE INGREDIENTS: CARBOXYMETHYLCELLULOSE SODIUM, UNSPECIFIED FORM; STEARIC ACID; POVIDONE, UNSPECIFIED; SODIUM STARCH GLYCOLATE TYPE A POTATO

Acetaminophen 325mg

Drug Facts

Active Ingredient (in each tablet)

Acetaminophen USP 325 mg

Purpose

Pain Reliever/ Fever Reducer

Uses

Temporary relieves minor aches and pains due to:

- The common cold
- Headache
- Backache
- Minor pain of arthritis
- Toothache
- Muscular aches
- Premenstrual and menstrual cramps

* Temporarily reduces fever.

Warnings

Liver warning: this product contains acetaminophen. The maximum daily dose of this product is 10 tablets (3,250 mg) in 24 hours. Severe liver damage may occur if you take

- more than 4,000 mg of acetaminophen in 24 hours
- with other drugs containing acetaminophen
- 3 or more alcoholic drinks every day while using this product

Do not use

- with any other drug containing acetaminophen (prescription or nonprescription). If you are not sure whether a drug contains acetaminophen, ask a doctor or pharmacist.
- if you are allergic to acetaminophen or any of the inactive ingredients in this product.

Drug Facts (continued)

Ask a doctor before use if you have liver disease .

Ask a doctor or pharmacist before use

if you are taking the blood thinning drug warfarin.

Stop use and ask a doctor if

- Pain gets worse or lasts more than 10 days.
- Fever gets worse or lasts more than 3 days.
- New symptoms occur.
- Redness or swelling is present.

These could be signs of a serious condition.

If pregnant or breast-feeding,

ask a health professional before use.

Overdose warning:

Taking more than the recommended dose (overdose) may cause liver damage. In case of overdose, get medical help or contact a Poison Control Center right away. (1-800-222-1222). Quick medical attention is critical for adults as well as for children even if you do not notice any signs or symptoms.

Directions

Do not take more than directed (see overdose warning)

Adults and Children 12 years and over:

- Take 2 tablets every 6 hours while symptoms last.
- Do not take more than 12 tablets in 24 hours, unless directed by a doctor.
- Do not use for more than 10 days unless directed by a doctor.

Children 6-11 years:

- Take 1 tablet every 4 to 6 hours while symptoms last.
- Do not take more than 5 tablets in 24 hours.

Children under 6 years:

- ask a doctor.

Other Information

- Store between 20-25 ˚C (68-77 ˚F).
- See end panel for lot number and expiration date.

Inactive Ingredients

Povidone, Pregelatinized Starch, Sodium Carboxymethyl Starch, Stearic Acid

Distributed by:
Marlex Pharmaceuticals, Inc.
New Castle, DE 19720

PRINCIPAL DISPLAY PANEL

NDC 10135-0123-01
Acetaminophen
325 mg
100 TABLETS